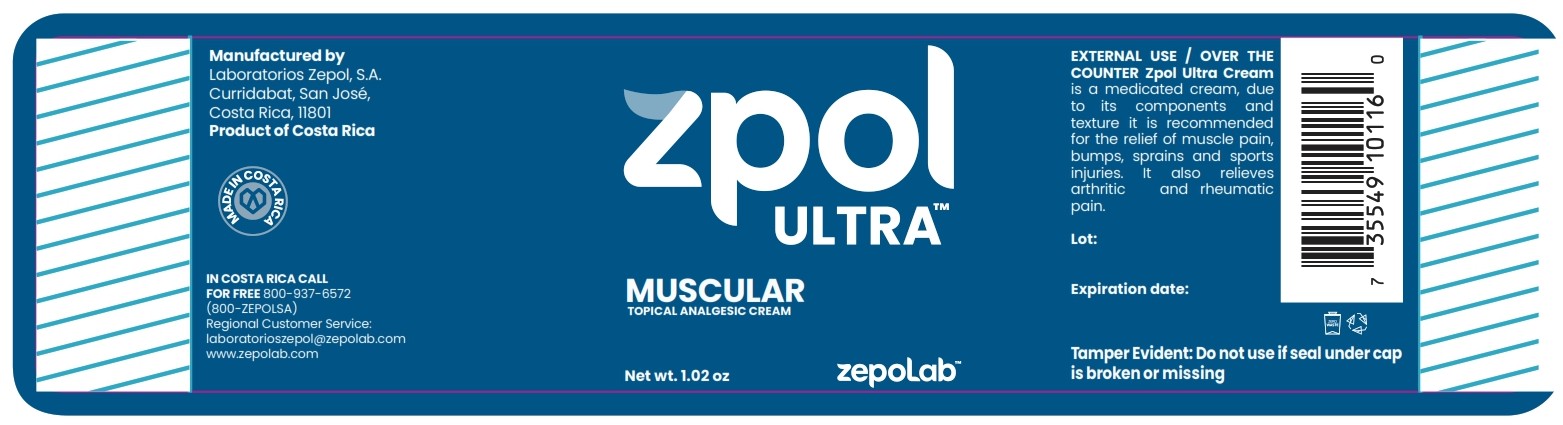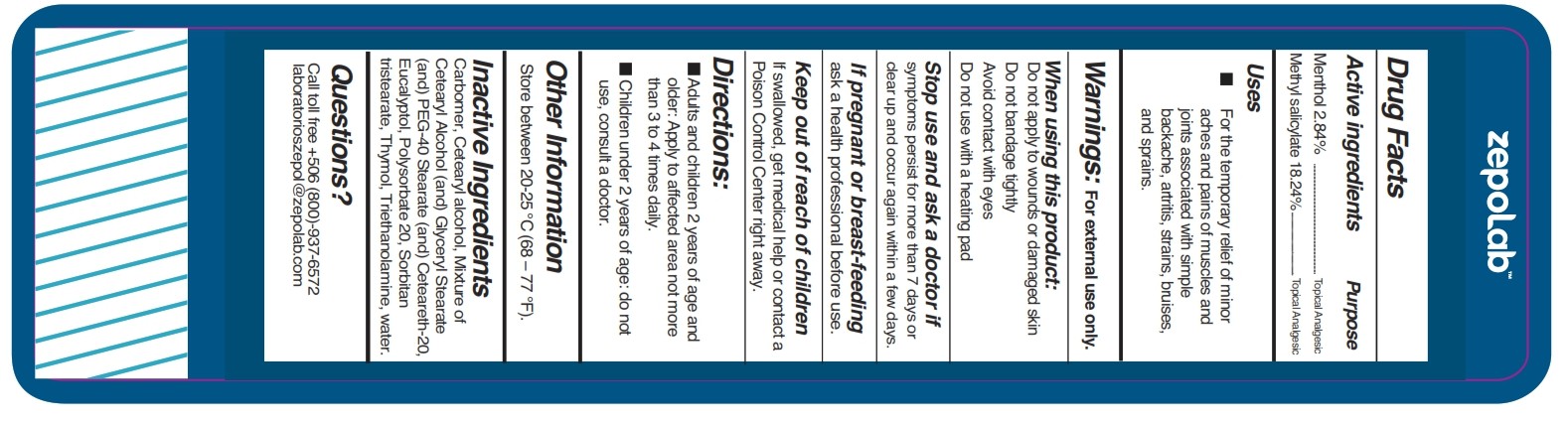 DRUG LABEL: Zpol ULTRA
NDC: 55715-008 | Form: CREAM
Manufacturer: Laboratorios Zepol S.A.
Category: otc | Type: HUMAN OTC DRUG LABEL
Date: 20250327

ACTIVE INGREDIENTS: MENTHOL 2.84 g/100 g; METHYL SALICYLATE 18.24 g/100 g
INACTIVE INGREDIENTS: SORBITAN TRISTEARATE; CARBOMER; CETEARYL ALCOHOL; GLYCERYL STEARATE; PEG-40 STEARATE; CETEARETH-20; EUCALYPTOL; POLYSORBATE 20; TRIETHANOLAMINE; THYMOL; WATER

Zpol Ultra

Active ingredients

Menthol 4%Methyl Salicylate 10%

Purpose

Active Ingredients | Purpose
Menthol 2.84% | Topical Analgesic
Methyl salicylate 18.24% | Topical Analgesic

Uses

For the temporary relief of minor aches and pains of muscles and joints associated with simple backache, arthritis, strains, bruises, and sprains.

Warnings

For external use only.

When using this product

Do not apply to wounds or damaged skin

Do not bandage tightly

Avoid contact with eyes

Do not use with a heating pad

Stop use and ask a doctor if

condition worsens, or if symptoms persist for more than 7 days or clear up and occur again within a few days.

If pregnant or breast-feeding

, ask a health professional before use.

Keep out of reach of children.

If swallowed, get medical help or contact a Poison Control Center right away.

Directions

Adults and children 2 years of age and older: Apply to affected area not more than 3 to 4 times daily.

Children under 2 years of age: Do not use, consult a doctor.

Other information

Store between 20-25°C (68-77°F).

Inactive ingredients

Allantoin, benzoic acid, cetearyl alcohol, cetearyl glucoside, pheonoxyethanol, stearic acid, water.

Questions?

Call toll free +506 (800)-937-6572 laboratorioszepol@zepolab.com

zpol ULTRA 1.02 Oz

NDC 55715-008-01

zpol ULTRA

MUSCULAR Topical analgesic cream

Net wt. 1.02 Oz

ZepoLAB

Manufactured by

Laboratorios Zepol, S.A.

Curridabat, San José,

Costa Rica, 11801

Product of Costa Rica

IN COSTA RICA CALL FRO FREE 800-937-6572

(800-SZEPOLSA)

Regional Customer Service:

laboratorioszepol@zepolab.com

www.zepolab.com

Tamper Evident: Do not use if seal undercap is broken or missing

EXTERNAL USE/OVER THE COUNTER Zpol ULTRA Cream

is a medicated cream, due to its components and texture it is recommended for the relief of muscle pain, bumps, sprains and sports injuries. It also relieves arthritic and rheumatic pain.

zpol ULTRA 2.08 Oz

NDC 55715-008-02

zpol ULTRA

Topical analgesic cream

2.08 Oz

ZepoLAB

Zpol ULTRA 4.02 Oz

NDC 55715-008-03

zpol ULTRA

Topical analgesic cream

4.02 Oz

ZepoLAB